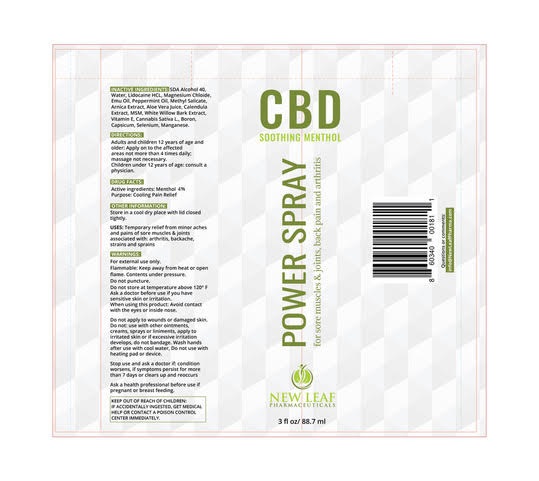 DRUG LABEL: RS
NDC: 71798-003 | Form: SPRAY
Manufacturer: New Leaf Pharmaceutical, LLC
Category: otc | Type: HUMAN OTC DRUG LABEL
Date: 20191007

ACTIVE INGREDIENTS: MENTHOL, UNSPECIFIED FORM 4 g/4 mL
INACTIVE INGREDIENTS: .ALPHA.-TOCOPHEROL ACETATE, DL-; WILLOW BARK; CALENDULA OFFICINALIS FLOWER; ARNICA MONTANA FLOWER; PEPPERMINT OIL; CANNABIDIOL; EMU OIL; METHYL SALICYLATE; CAPSICUM ANNUUM WHOLE

CBD Power Spray